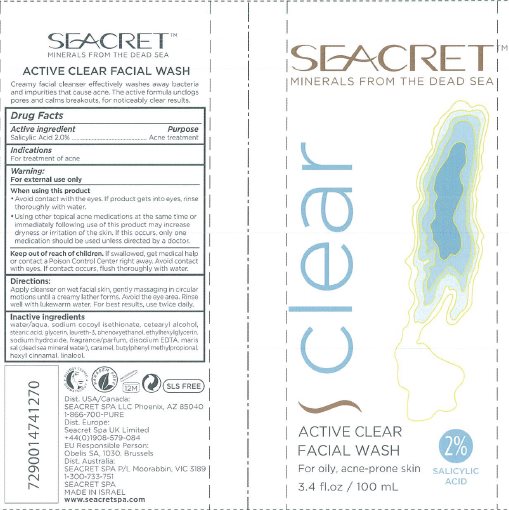 DRUG LABEL: Seacret Active Clear Facial Wash
NDC: 42421-290 | Form: GEL
Manufacturer: Emilia Personal Care Inc.
Category: otc | Type: HUMAN OTC DRUG LABEL
Date: 20141015

ACTIVE INGREDIENTS: SALICYLIC ACID 2 g/100 mL
INACTIVE INGREDIENTS: WATER; SODIUM COCOYL ISETHIONATE; CETOSTEARYL ALCOHOL; STEARIC ACID; GLYCERIN; LAURETH-3; PHENOXYETHANOL; ETHYLHEXYLGLYCERIN; SODIUM HYDROXIDE; EDETATE DISODIUM; CARAMEL; BUTYLPHENYL METHYLPROPIONAL; .ALPHA.-HEXYLCINNAMALDEHYDE; LINALOOL, (+/-)-

Seacret™ Active Clear Facial Wash

Active ingredient

Salicylic Acid 2.0%

Purpose

Acne treatment

Indications

For treatment of acne

Warnings

For external use only

When using this product

- Avoid contact with the eyes. If product gets into eyes, rinse thoroughly with water.
- Using other topical acne medications at the same time or immediately following use of this product may increase dryness or irritation of the skin. If this occurs, only one medication should be used unless directed by a doctor.

Keep Out of Reach of Children.

If swallowed, get medical help or contact a Poison Control Center right away. Avoid contact with eyes. If contact occurs, flush thoroughly with water.

Directions

Apply cleanser on wet facial skin, gently massaging in circular motions until a creamy lather forms. Avoid the eye area. Rinse well with lukewarm water. For best results, use twice daily.

Inactive ingredients

water/aqua, sodium cocoyl isethionate, cetearyl alcohol, stearic acid, glycerin, laureth-3, phenoxyethanol, ethylhexylglycerin, sodium hydroxide, fragrance/parfum, disodium EDTA, maris sal (dead sea mineral water), caramel, butylphenyl methylpropional, hexyl cinnamal, linalool.

Package/Label Principal Display Panel

SEACRET™
MINERALS FROM THE DEAD SEA

clear

ACTIVE CLEAR
FACIAL WASH

For oily, acne-prone skin

2%
SALICYLIC
ACID

3.4 fl.oz / 100 mL

SEACRET™
MINERALS FROM THE DEAD SEA

ACTIVE CLEAR FACIAL WASH

Creamy facial cleanser effectively washes away bacteria and impurities that cause acne. The active formula unclogs pores and calms breakouts, for noticeably clear results.

ALLERGY TESTED
DERMATOLOGY

PARABEN FREE

12M

SLS FREE

Dist. USA/Canada:
SEACRET SPA LLC Phoenix, AZ 85040
1-866-700-PURE
Dist. Europe:
Seacret Spa UK Limited
+44(0)1908-579-084
EU Responsible Person:
Obelis SA, 1030, Brussels
Dist. Australia:
SEACRET SPA P/L Moorabbin, VIC 3189
1-300-733-751
SEACRET SPA
MADE IN ISRAEL
www.seacretspa.com

Carton Label